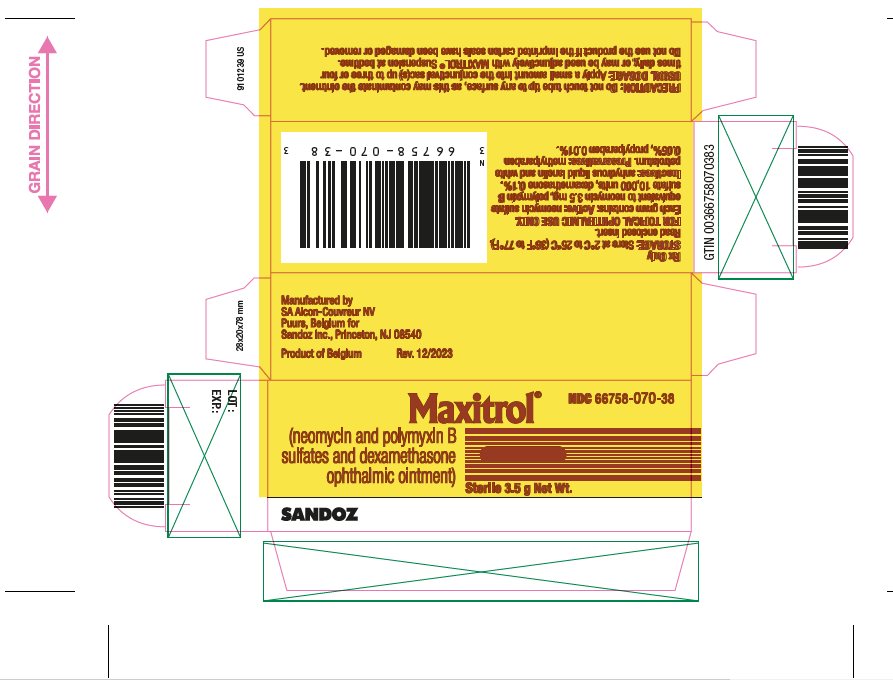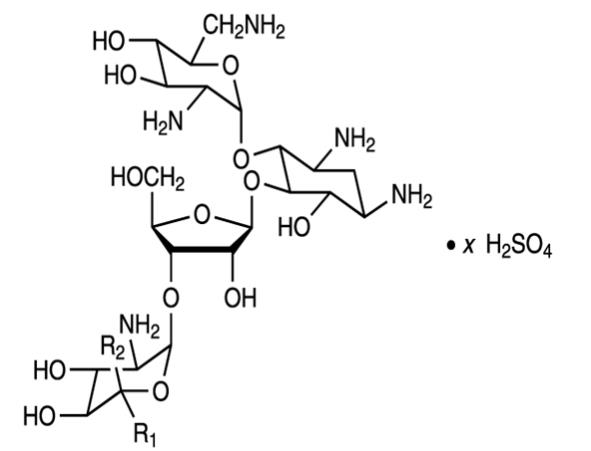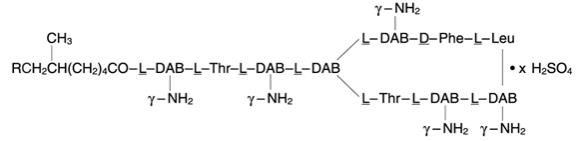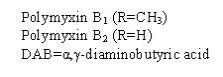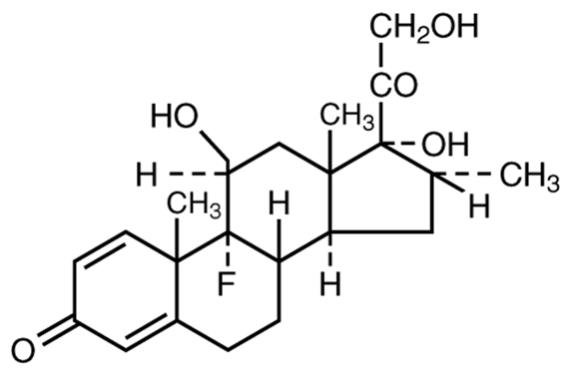 DRUG LABEL: MAXITROL
NDC: 66758-070 | Form: OINTMENT
Manufacturer: Sandoz Inc
Category: prescription | Type: HUMAN PRESCRIPTION DRUG LABEL
Date: 20231229

ACTIVE INGREDIENTS: NEOMYCIN SULFATE 3.5 mg/1 g; POLYMYXIN B SULFATE 10000 [USP'U]/1 g; DEXAMETHASONE 1 mg/1 g
INACTIVE INGREDIENTS: METHYLPARABEN; PROPYLPARABEN; PETROLATUM; LANOLIN

Maxitrol Ointment

MAXITROL® (neomycin and polymyxin B sulfates and dexamethasone ophthalmic ointment) Sterile

DESCRIPTION

MAXITROL® (neomycin and polymyxin B sulfates and dexamethasone ophthalmic ointment) is a multiple dose anti-infective steroid combination in sterile ointment form for topical application. The chemical structure for the active ingredient Neomycin Sulfate is:

Neomycin B (R1=H, R2=CH2NH2)

Neomycin C (R1=CH2NH2, R2=H)

The chemical structure for the active ingredient Polymyxin B Sulfate is:

The chemical structure for the active ingredient dexamethasone is:

C22H29FO5

Molecular Weight = 392.47 g/mol

Established name: dexamethasone

Chemical name: pregna-1, 4-diene-3, 20-dione,9-fluoro-11,17, 21-trihydroxy-16-methyl-, (11β, 16α)-.

Each gram of MAXITROL® (neomycin and polymyxin B sulfates and dexamethasone ophthalmic ointment) contains: Active: neomycin sulfate equivalent to neomycin 3.5 mg, polymyxin B sulfate 10,000 units, dexamethasone 0.1%. Inactives: anhydrous liquid lanolin and white petrolatum. Preservatives: methylparaben 0.05%, propylparaben 0.01%.

CLINICAL PHARMACOLOGY

Corticosteroids suppress the inflammatory response to a variety of agents and they probably delay or slow healing. Since corticosteroids may inhibit the body's defense mechanism against infection, a concomitant antimicrobial drug may be used when this inhibition is considered to be clinically significant in a particular case.

When a decision to administer both a corticosteroid and an antimicrobial is made, the administration of such drugs in combination has the advantage of greater patient compliance and convenience, with the added assurance that the appropriate dosage of both drugs is administered, plus assured compatibility of ingredients when both types of drugs are in the same formulation and, particularly, that the correct volume of drug is delivered and retained.

The relative potency of corticosteroids depends on the molecular structure, concentration and release from the vehicle.

INDICATIONS AND USAGE

For steroid-responsive inflammatory ocular conditions for which a corticosteroid is indicated and where bacterial infection or a risk of bacterial ocular infection exists.

Ocular steroids are indicated in inflammatory conditions of the palpebral and bulbar conjunctiva, cornea, and anterior segment of the globe where the inherent risk of steroid use in certain infective conjunctivitides is accepted to obtain a diminution in edema and inflammation. They are also indicated in chronic anterior uveitis and corneal injury from chemical, radiation or thermal burns; or penetration of foreign bodies.

The use of a combination drug with an anti-infective component is indicated where the risk of infection is high or where there is an expectation that potentially dangerous numbers of bacteria will be present in the eye.

The particular anti-infective drug in this product is active against the following common bacterial eye pathogens: Staphylococcus aureus, Escherichia coli, Haemophilus influenzae, Klebsiella/Enterobacter species, Neisseria species, and Pseudomonas aeruginosa.

This product does not provide adequate coverage against: Serratia marcescens and Streptococci, including Streptococcus pneumoniae.

CONTRAINDICATIONS

MAXITROL® (neomycin and polymyxin B sulfates and dexamethasone ophthalmic ointment) is contraindicated in epithelial herpes simplex keratitis (dendritic keratitis), vaccinia, varicella, and many other viral diseases of the cornea and conjunctiva. Mycobacterial infection of the eye. Fungal diseases of ocular structures. MAXITROL (neomycin and polymyxin B sulfates and dexamethasone ophthalmic ointment) is also contraindicated in individuals with known or suspected hypersensitivity to a component of the medication. (Hypersensitivity to the antibiotic component occurs at a higher rate than for other components.)

WARNINGS

NOT FOR INJECTION. Use of ocular steroids may prolong the course and may exacerbate the severity of many viral infections of the eye (including herpes simplex). Employment of steroid medication in the treatment of herpes simplex requires great caution; frequent slit lamp microscopy is recommended.

Prolonged use may result in glaucoma, with damage to the optic nerve, defects in visual acuity and fields of vision, and posterior subcapsular cataract formation. Prolonged use may suppress the host response and thus increase the hazard of secondary ocular infections. In acute purulent conditions or parasitic infections of the eye, steroids may mask infection or enhance existing infection.

In those diseases causing thinning of the cornea or sclera, perforations have been known to occur with the use of topical steroids.

If this product is used for 10 days or longer, intraocular pressure (IOP) should be routinely monitored even though it may be difficult in children and uncooperative patients. Steroids should be used with caution in the presence of glaucoma. IOP should be checked frequently.

The use of steroids after cataract surgery may delay healing and increase the incidence of bleb formation.

Products containing neomycin sulfate may cause cutaneous sensitization. Sensitivity to topically administered aminoglycosides, such as neomycin, may occur in some patients. Severity of hypersensitivity reactions may vary from local effects to generalized reactions such as erythema, itching, urticaria, skin rash, anaphylaxis, anaphylactoid reactions, or bullous reactions. If hypersensitivity develops during use of the product, treatment should be discontinued. Cross-hypersensitivity to other aminoglycosides can occur, and the possibility that patients who become sensitized to topical neomycin may also be sensitive to other topical and/or systemic aminoglycosides should be considered.

PRECAUTIONS

General

The initial prescription and renewal of the medication order beyond 8 g of MAXITROL® (neomycin and polymyxin B sulfates and dexamethasone ophthalmic ointment) should be made by a physician only after examination of the patient with the aid of magnification, such as a slit lamp biomicroscopy and, where appropriate, fluorescein staining.

The possibility of persistent fungal infections of the cornea should be considered after prolonged steroid dosing. Fungal infection should be suspected in patients with persistent corneal ulceration.

Information for Patients

If inflammation or pain persists longer than 48 hours or becomes aggravated, the patient should be advised to discontinue use of the medication and consult a physician.

This product is sterile when packaged. To prevent contamination, care should be taken to avoid touching the tube tip to eyelids or to any other surface. The use of this tube by more than one person may spread infection. Keep tube tightly closed when not in use. Keep out of reach of children.

Patients should be advised that their vision may be temporarily blurred following dosing with MAXITROL (neomycin and polymyxin B sulfates and dexamethasone ophthalmic ointment). Care should be exercised in operating machinery or driving a motor vehicle.

Carcinogenesis, Mutagenesis, Impairment of Fertility

Long-term studies in animals to evaluate carcinogenic or mutagenic potential have not been conducted with polymyxin B sulfate. Treatment of cultured human lymphocytes in vitro with neomycin increased the frequency of chromosome aberrations at the highest concentration (80 mcg/mL) tested. However, the effects of neomycin on carcinogenesis and mutagenesis in humans are unknown. Polymyxin B has been reported to impair the motility of equine sperm, but its effects on male or female fertility are unknown.

Pregnancy

Dexamethasone has been shown to be teratogenic in mice and rabbits following topical ophthalmic application in multiples of the therapeutic dose.

In the mouse, corticosteroids produce fetal resorptions and a specific abnormality, cleft palate. In the rabbit, corticosteroids have produced fetal resorptions and multiple abnormalities involving the head, ears, limbs, palate, etc.

There are no adequate or well-controlled studies in pregnant women. However, prolonged or repeated corticoid use during pregnancy has been associated with an increased risk of intra-uterine growth retardation. MAXITROL® (neomycin and polymyxin B sulfates and dexamethasone ophthalmic ointment) should be used during pregnancy only if the potential benefit to the mother justifies the potential risk to the embryo or fetus. Infants born of mothers who have received substantial doses of corticosteroids during pregnancy should be observed carefully for signs of hypoadrenalism.

Nursing Mothers

Systemically administered corticosteroids appear in human milk, could suppress growth, interfere with endogenous corticosteroid production, or cause other untoward effects. It is not known whether topical administration of corticosteroids could result in sufficient systemic absorption to produce detectable quantities in human milk. Because many drugs are excreted in human milk, caution should be exercised when MAXITROL® (neomycin and polymyxin B sulfates and dexamethasone ophthalmic ointment) is administered to a nursing woman.

Pediatric Use

Safety and effectiveness in pediatric patients have not been established.

Geriatric Use

No overall clinical differences in safety or effectiveness have been observed between the elderly and other adult patients.

ADVERSE REACTIONS

Adverse reactions have occurred with steroid/anti-infective combination drugs which can be attributed to the steroid component, the anti-infective component, or the combination. Exact incidence figures are not available since no denominator of treated patients is available.

Reactions occurring most often from the presence of the anti-infective ingredient are allergic sensitizations. The reactions due to the steroid component are: elevation of IOP with possible development of glaucoma, and infrequent optic nerve damage; posterior subcapsular cataract formation; and delayed wound healing.

Secondary Infection: The development of secondary infection has occurred after use of combinations containing steroids and antimicrobials. Fungal infections of the cornea are particularly prone to develop coincidentally with long-term applications of steroid. The possibility of fungal invasion must be considered in any persistent corneal ulceration where steroid treatment has been used. Keratitis, conjunctivitis, corneal ulcers, and conjunctival hyperemia have occasionally been reported following use of steroids. Secondary bacterial ocular infection following suppression of host responses also occurs.

Additional adverse reactions identified from post marketing use include ulcerative keratitis, headache, and Stevens-Johnson syndrome.

The following additional adverse reactions have been reported with dexamethasone use:

Cushing’s syndrome and adrenal suppression may occur after use of dexamethasone in excess of the listed dosing instructions in predisposed patients, including children and patients treated with CYP3A4 inhibitors.

DOSAGE AND ADMINISTRATION

Apply a small amount into the conjunctival sac(s) up to three or four times daily.

How to Apply MAXITROL® (neomycin and polymyxin B sulfates and dexamethasone ophthalmic ointment):

1. Tilt your head back.

2. Place a finger on your cheek just under your eye and gently pull down until a "V" pocket is formed between your eyeball and your lower lid.

3. Place a small amount (about ½ inch) of MAXITROL (neomycin and polymyxin B sulfates and dexamethasone ophthalmic ointment) in the "V" pocket. Do not let the tip of the tube touch your eye.

4. Look downward before closing your eye.

Not more than 8 g should be prescribed initially and the prescription should not be refilled without further evaluation as outlined in PRECAUTIONS above.

HOW SUPPLIED

MAXITROL® (neomycin and polymyxin B sulfates and dexamethasone ophthalmic ointment) is supplied as a STERILE ointment in an aluminum tube with a white polyethylene tip and white polyethylene cap as follows:

3.5 g in an aluminum tube NDC 66758-070-38

Storage: Store at 2°C to 25°C (36°F to 77°F).

After opening, MAXITROL (neomycin and polymyxin B sulfates and dexamethasone ophthalmic ointment) can be used until the expiration date on the tube.

Manufactured by

SA Alcon-Couvreur NV

Puurs, Belgium for

Sandoz Inc., Princeton, NJ 08540

Revised: December 2023

9101235 US

PRINCIPAL DISPLAY PANEL

NDC 66758-070-38

Maxitrol®

(neomycin and polymyxin B

sulfates and dexamethasone

ophthalmic ointment)

Sterile 3.5 g Net Wt.

Rx Only

SANDOZ